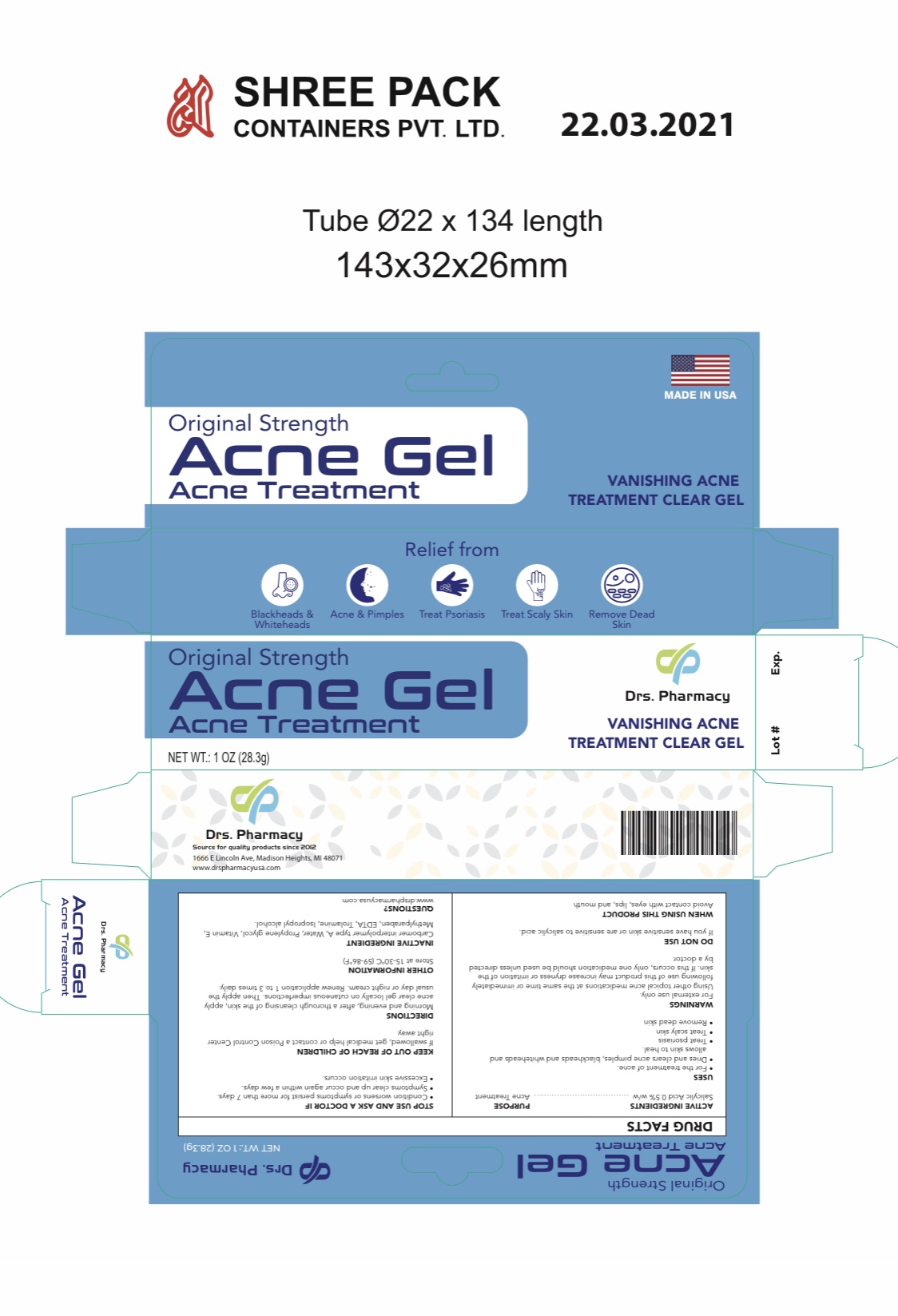 DRUG LABEL: Drs. ACNE CLEAR
NDC: 80489-300 | Form: GEL
Manufacturer: OL PHARMA TECH, LLC Drs. PHARMACY
Category: otc | Type: HUMAN OTC DRUG LABEL
Date: 20250109

ACTIVE INGREDIENTS: SALICYLIC ACID 5 mg/1 g
INACTIVE INGREDIENTS: CARBOMER INTERPOLYMER TYPE A (55000 CPS); WATER; PROPYLENE GLYCOL; .ALPHA.-TOCOPHEROL; METHYLPARABEN; EDETATE DISODIUM; TROLAMINE; ISOPROPYL ALCOHOL

ACTIVE INGREDIENT

Salicylic Acid 0.5% w/w.

PURPOSE

Acne treatment

RECENT MAJOR CHANGES

For treatment of acne.Dries and clears acne pimples

USES

For the treatment of acne. Dries and clears acne pimples

DO NOT USE

if you have sensitive skin or are sensitive to salicylic acid

DIRECTIONS

Morning and evening, after a thorough cleansing of the skin, apply acne clear gel locally on cutanous imperfections. Then apply the usual day or night cream. Renew application 1 to 3 times daily.

WARNINGS

For external use only. Using other topical acne medications at the same time or immediately following use of this product may increase dryness or irritation of the skin. If this occurs, only one medication should be used unless directed by a doctor. Avoid direct contact with the eyes. If product gets into the eyes, rinse liberally with water. Discontinue use if skin irritation develops or increases. If irritation persists, consult a doctor.

WHEN USING THIS PRODUCT

Avoid contact with eyes, lips, and mouth.

KEEP OUT OF REACH OF CHILDREN

if swallowed, get medical help or contact poison control center right away

INACTIVE INGREDIENT

carbomer interpolymer type A, trolamine, vitamin E, propylene glycol, water, isopropyl alcohol, methyl paraben, EDTA, propyl paraben, DMDM hydantoin

OTHER INFORMATION

- store at 15-30 C (59-86 F)
- close cap tightly after use
- keep away from heat

QUESTIONS

www.drspharmacyusa.com